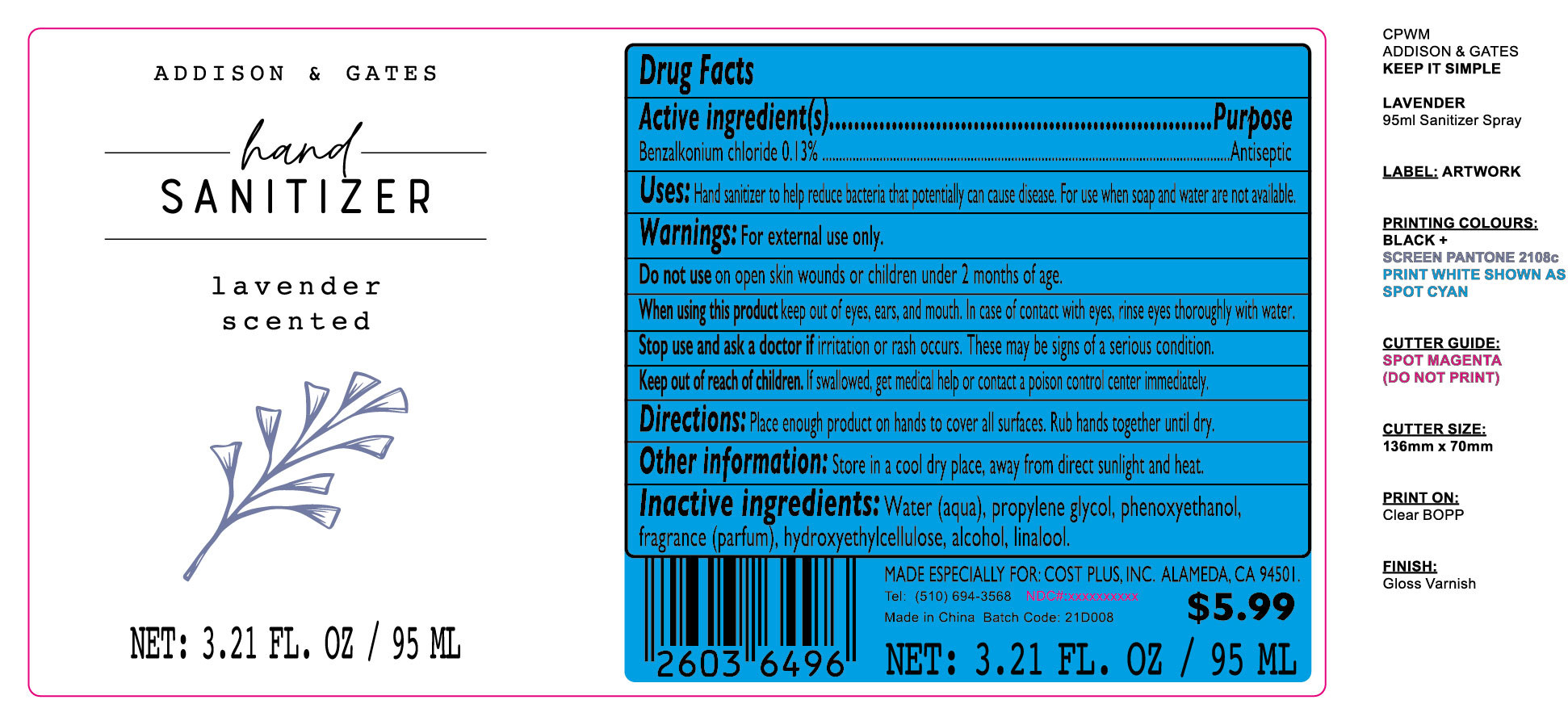 DRUG LABEL: Hand Sanitizer
NDC: 81726-006 | Form: GEL
Manufacturer: The Source Design Collections
Category: otc | Type: HUMAN OTC DRUG LABEL
Date: 20210416

ACTIVE INGREDIENTS: BENZALKONIUM CHLORIDE 0.1235 g/95 mL
INACTIVE INGREDIENTS: FRAGRANCE EUCALYPTUS SPEARMINT ORC1601627; WATER; HYDROXYETHYL CELLULOSE, UNSPECIFIED; PHENOXYETHANOL; ALCOHOL; PROPYLENE GLYCOL; LINALOOL, (+/-)-

ACTIVE INGREDIENT

Benzalkonium Chloride 0.13%

PURPOSE

Antiseptic

Uses

Hand sanitizer to help reduce bacteria that potentially can cause disease. For use when soap and water are not available.

INACTIVE INGREDIENT

Water (aqua), propylene glycol, phenoxyethanol,fragrance (parfum), hydroxyethylcellulose, alcohol, linalool.

Directions

Place enough product on hands to cover all surfaces.Rub hands together until dry.

WARNINGS

For external use only.

Do not use on open skin wounds or children under 2 months of age.

When using this product keep out of eyes,ears, and mouth. ln case of contact with eyes,rinse eyes thoroughly with water.

Stop use and ask a doctor if irritation or rash occurs.These may be signs of a serious condition.

Keep out of reach of children. If swallowed, get medical help or contact a poison control center immediately.

Other information

Store in a cool dry place, away from direct sunlight and heat.